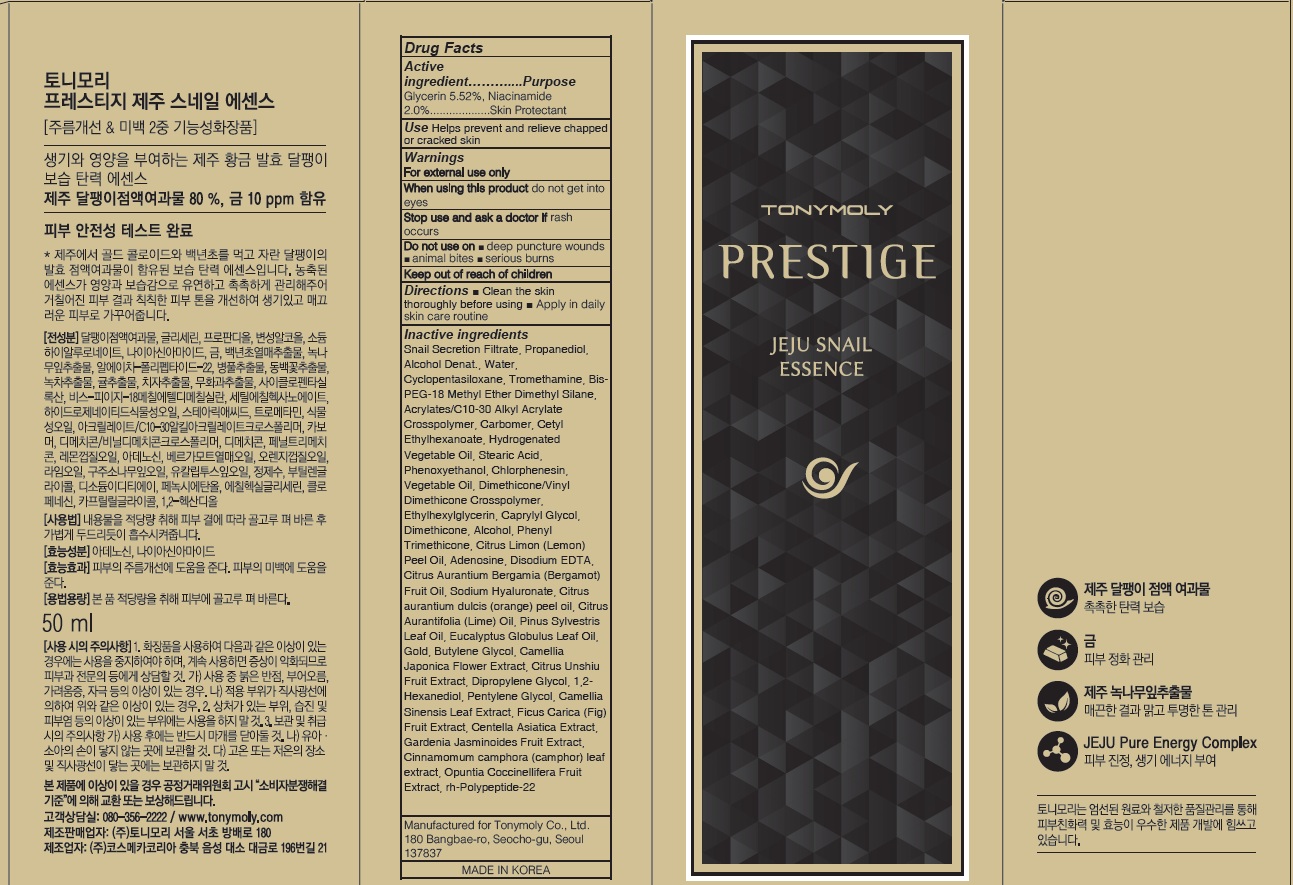 DRUG LABEL: PRESTIGE JEJU SNAIL ESSENCE
NDC: 59078-319 | Form: CREAM
Manufacturer: TONYMOLY CO.,LTD
Category: otc | Type: HUMAN OTC DRUG LABEL
Date: 20160729

ACTIVE INGREDIENTS: Glycerin 2.76 g/50 mL; Niacinamide 1.0 g/50 mL
INACTIVE INGREDIENTS: Propanediol; Water

ACTIVE INGREDIENT

Active Ingredient: Glycerin 5.52%, Niacinamide 2.0%

INACTIVE INGREDIENT

Inactive Ingredients: Snail Secretion Filtrate, Propanediol, Alcohol Denat., Water, Cyclopentasiloxane, Tromethamine, Bis-PEG-18 Methyl Ether Dimethyl Silane, Acrylates/C10-30 Alkyl Acrylate Crosspolymer, Carbomer, Cetyl Ethylhexanoate, Hydrogenated Vegetable Oil, Stearic Acid, Phenoxyethanol, Chlorphenesin, Vegetable Oil, Dimethicone/Vinyl Dimethicone Crosspolymer, Ethylhexylglycerin, Caprylyl Glycol, Dimethicone, Alcohol, Phenyl Trimethicone, Citrus Limon (Lemon) Peel Oil, Adenosine, Disodium EDTA, Citrus Aurantium Bergamia (Bergamot) Fruit Oil, Sodium Hyaluronate, Citrus aurantium dulcis (orange) peel oil, Citrus Aurantifolia (Lime) Oil, Pinus Sylvestris Leaf Oil, Eucalyptus Globulus Leaf Oil, Gold, Butylene Glycol, Camellia Japonica Flower Extract, Citrus Unshiu Fruit Extract, Dipropylene Glycol, 1,2-Hexanediol, Pentylene Glycol, Camellia Sinensis Leaf Extract, Ficus Carica (Fig) Fruit Extract, Centella Asiatica Extract, Gardenia Jasminoides Fruit Extract, Cinnamomum camphora (camphor) leaf extract, Opuntia Coccinellifera Fruit Extract, rh-Polypeptide-22

PURPOSE

Purpose: Skin Protectant

WARNINGS

Warnings: For external use only When using this product do not get into eyes, Stop use and ask a doctor if rash occurs Do not use on - deep puncture wounds - animal bites - serious burns Keep out of reach of children

KEEP OUT OF REACH OF CHILDREN

Use

Use: Helps prevent and relieve chapped or cracked skin

Directions

Directions: - Clean the skin thoroughly before using - Apply in daily skin care routine